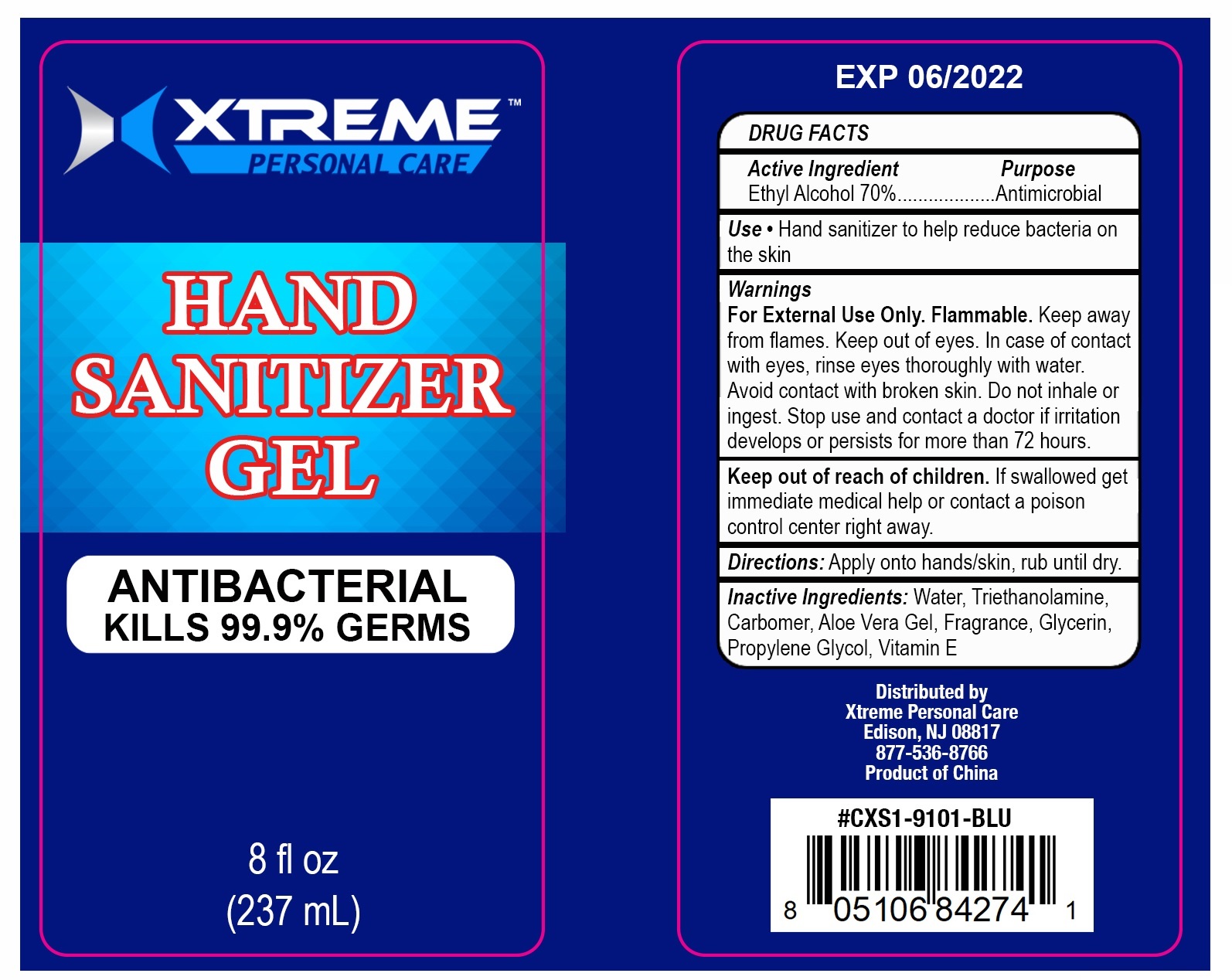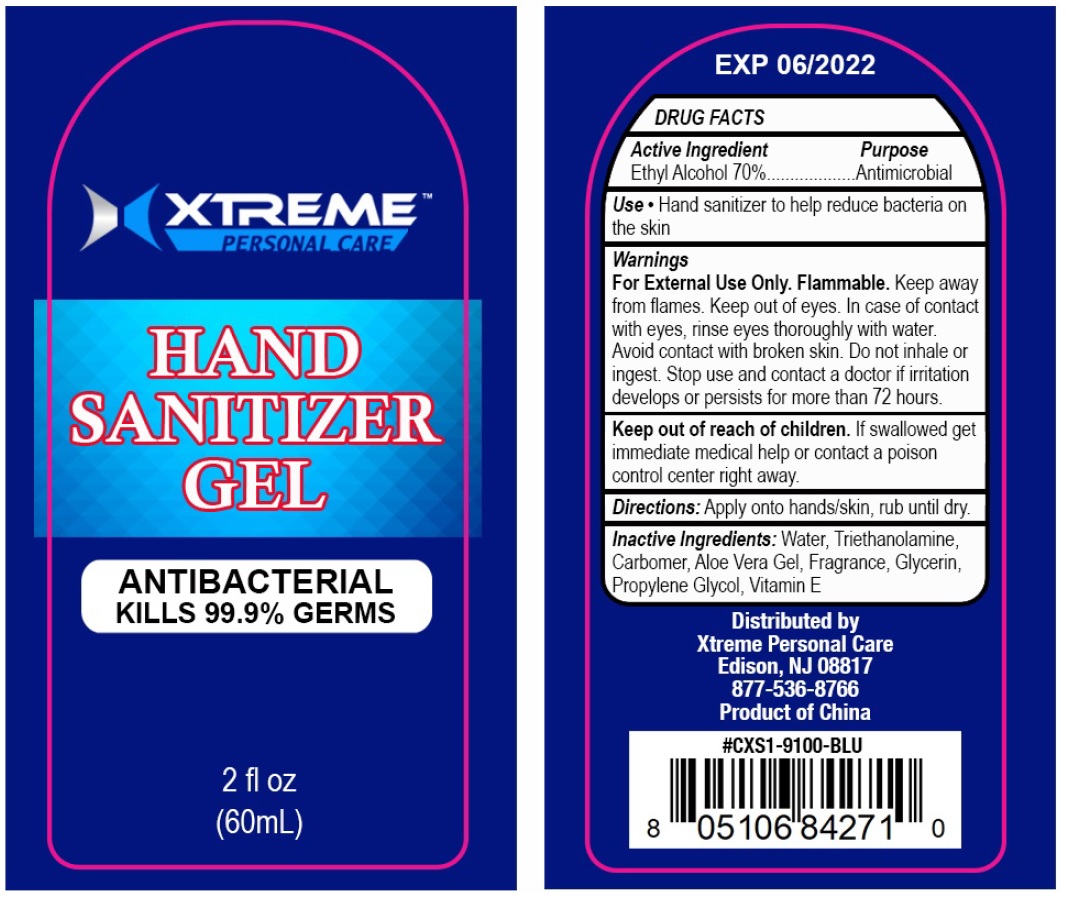 DRUG LABEL: Xtreme Hand Sanitizer
NDC: 74851-001 | Form: GEL
Manufacturer: Xtreme Personal Care Inc
Category: otc | Type: HUMAN OTC DRUG LABEL
Date: 20220107

ACTIVE INGREDIENTS: ALCOHOL 0.7 mL/1 mL
INACTIVE INGREDIENTS: WATER; TROLAMINE; CARBOMER HOMOPOLYMER, UNSPECIFIED TYPE; ALOE VERA LEAF; GLYCERIN; PROPYLENE GLYCOL; .ALPHA.-TOCOPHEROL

Xtreme Hand Sanitizer Gel

Active ingredient

Ethyl Alcohol 70%

Purpose

Antimicrobial

Use

- Hand sanitizer to help reduce bacteria on the skin

Warnings

For External Use Only. Flammable.

WHEN USING

Keep away from flames. Keep out of eyes. In case of contact with eyes, rinse eyes thoroughly with water. Avoid contact with broken skin. Do not inhale or ingest.

Stop use and contact a doctor if irritation develops or persists for more than 72 hours.

Keep out of reach of children.

If swallowed get immediate help or contact a poison control center right away.

Directions:

Apply to hands/skin, rub until dry.

Inactive Ingredients

Water (Aqua), Acrylates/C10-30 Alkyl Acrylate Crosspolymer, Aloe Barbadensis Leaf Extract, Fragrance (Parfum), Triethanolamine, Tocopheryl Acetate (Vitamin E), Retinyl Palmitate (Vitamin A)